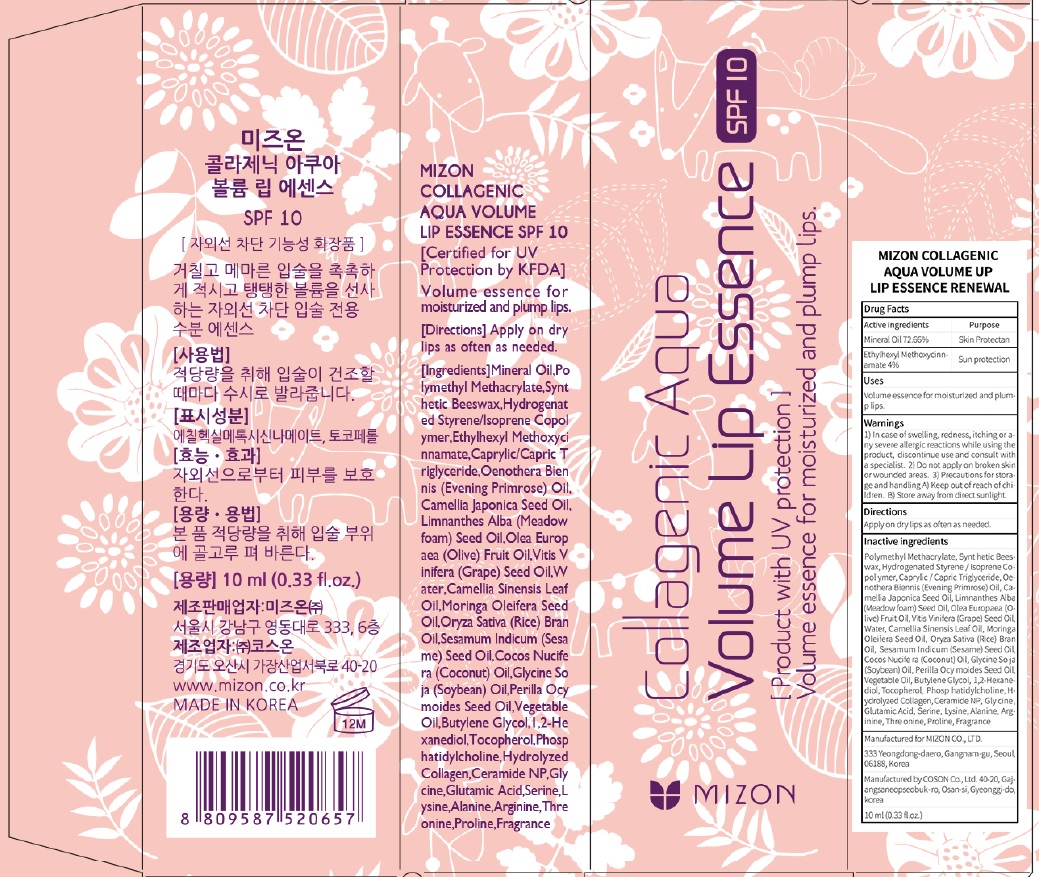 DRUG LABEL: MIZON COLLAGENIC AQUA VOLUME UP LI P ESSENCE RENEWAL
NDC: 57718-340 | Form: LIQUID
Manufacturer: MIZON CO.,LTD.
Category: otc | Type: HUMAN OTC DRUG LABEL
Date: 20180726

ACTIVE INGREDIENTS: Mineral Oil 7.26 g/10 mL; Octinoxate 0.40 g/10 mL
INACTIVE INGREDIENTS: Butylene Glycol; 1,2-Hexanediol

ACTIVE INGREDIENT

Active ingredients: Mineral Oil 72.66%, Ethylhexyl Methoxycinnamate 4%

INACTIVE INGREDIENT

Inactive ingredients:

Polymethyl Methacrylate,Synt hetic Beeswax,Hydrogenated Styrene/Isoprene Copol ymer,Caprylic/Capric Triglyceride,Oenothera Biennis (Evening Primrose) Oil, Camellia Japonica Seed Oil, Limnanthes Alba (Meadow foam) Seed Oil,Olea Europ aea (Olive) Fruit Oil,Vitis Vinifera (Grape) Seed Oil,W ater,Camellia Sinensis Leaf Oil,Moringa Oleifera Seed Oil,Oryza Sativa (Rice) Bran Oil,Sesamum Indicum (Sesa me) Seed Oil,Cocos Nucife ra (Coconut) Oil,Glycine So ja (Soybean) Oil,Perilla Ocy moides Seed Oil,Vegetable Oil,Butylene Glycol,1,2-Hexanediol,Tocopherol,Phosp hatidylcholine,Hydrolyzed Collagen,Ceramide NP,Gly cine,Glutamic Acid,Serine,L ysine,Alanine,Arginine,Thre onine,Proline,Fragrance

PURPOSE

Purpose: Skin Protectant, Sun protection

WARNINGS

1) In case of swelling, redness, itching or any severe allergic reactions while using the product, discontinue use and consult with a specialist. 2) Do not apply on broken skin or wounded areas. 3) Precautions for storage and handling A) Keep out of reach of children. B) Store away from direct sunlight.

KEEP OUT OF REACH OF CHILDREN

Uses

Volume essence for moisturized and plump lips.

Directions

Apply on dry lips as often as needed.